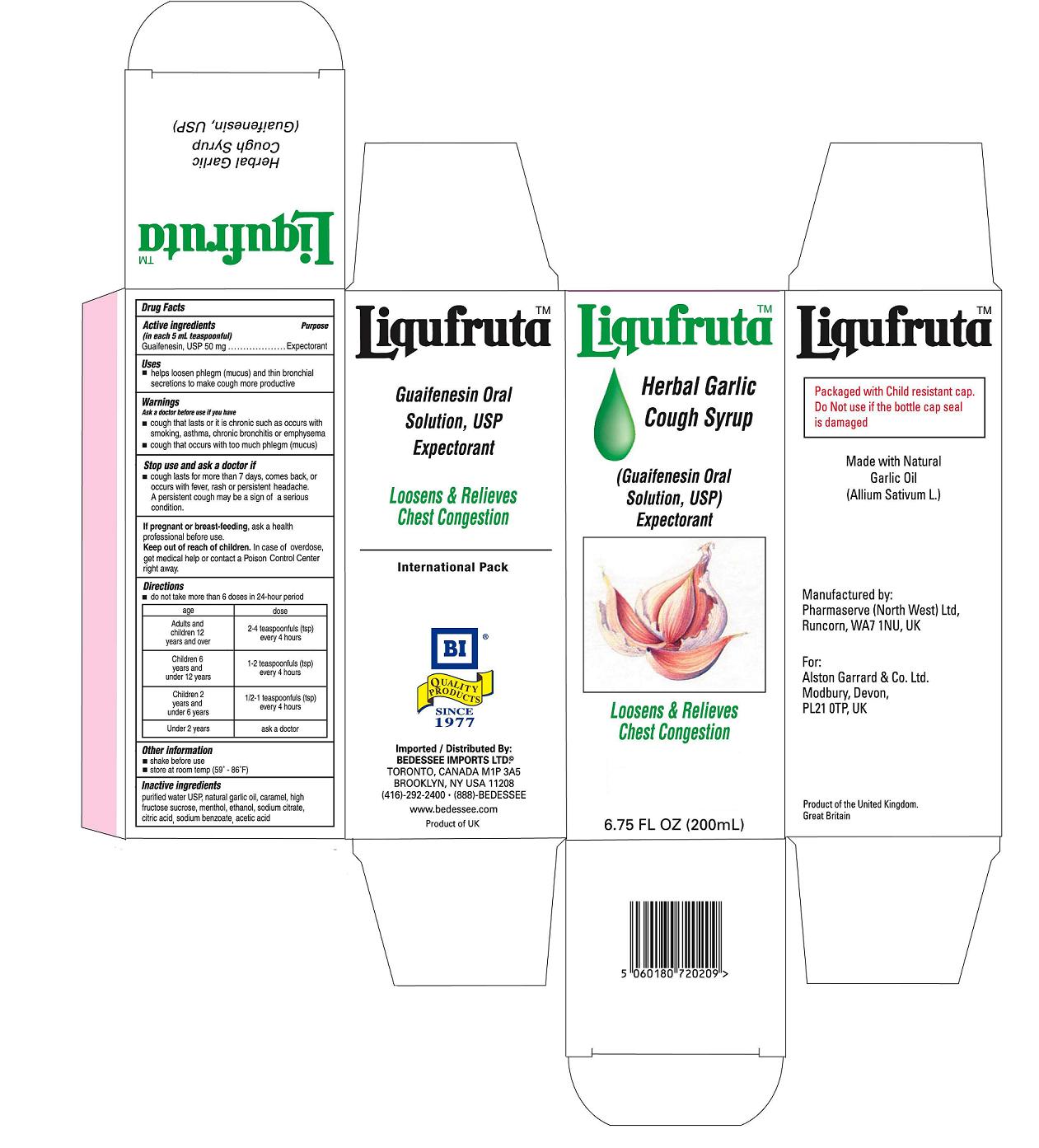 DRUG LABEL: Liqufruta
NDC: 75939-9876 | Form: SYRUP
Manufacturer: Alston Garrard & Co
Category: otc | Type: HUMAN OTC DRUG LABEL
Date: 20120530

ACTIVE INGREDIENTS: GUAIFENESIN 50 mg/5 mL
INACTIVE INGREDIENTS: WATER; ALCOHOL; SODIUM CITRATE; GARLIC OIL; CITRIC ACID MONOHYDRATE; HIGH FRUCTOSE CORN SYRUP; SODIUM BENZOATE; CARAMEL; MENTHOL; ACETIC ACID

Liqufruta Herbal Garlic Cough Syrup Guaifenensin Oral Solution,USP

ACTIVE INGREDIENT

GUAIFENESIN 50 MG/TEASPOON (5ML)

PURPOSE

EXPECTORANT -HELPS LOOSEN PHLEGM (MUCUS) AND THIN BRONCHIAL SECRETIONS TO MAKE COUGH MORE PRODUCTIVE

KEEP OUT OF REACH OF CHILDREN

Keep out reach of children. In case of overdose, get medical help or contact a Poison Control Center right away.

INDICATIONS AND USAGE

Loosens and Relieves Chest congestion

Ask a doctor before use if you have a cough that last or it is chronic such as occurs with smoking, asthma, chronic Bronchitis or emphysema. Stop use and ask doctor if a cough lasts for more than 7 days comes back or occurs when fever, rash or persistent headache. A persistent cough may be a sign of a serious condition.
If pregnant of breast-feeding, ask a health professional before use.

DOSAGE AND ADMINISTRATION

do not take more than 6 doses in a 24-hour period
AGE ......................................................DOSE
Adults and Children 12 years and over .......2-4 teaspoonfuls(tsp) every 4 hours
Children 6 years and under 12 years......... 1-2 teaspoonfuls(tsp) every 4 hours
Children 2 years and under 6 years........... 1/2-1 teaspoonfuls(tsp) every 4 hours
Under 2 years ........................................ask a doctor

INACTIVE INGREDIENT

Purified water, natural garlic oil,caramel, high fructose sucrose, menthol, ethanol, sodium citrate, citric acid, sodium benzoate, acetic acid

OTHER Information
Shake well Before Use
store at room temp (59F-86)
imported and Distributed by:
Bedessee Imports Ltd.
Brooklyn, NY USA 11208
1-888-BEDESSEE
416-292-2400